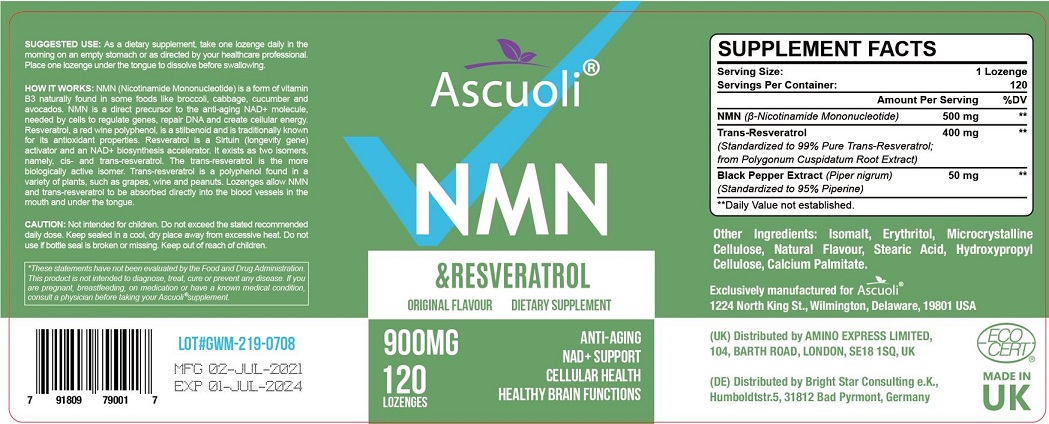 DRUG LABEL: Ascuoli
NDC: 83459-002 | Form: LOZENGE
Manufacturer: HEALGROW INC
Category: otc | Type: HUMAN OTC DRUG LABEL
Date: 20230526

ACTIVE INGREDIENTS: RESVERATROL 400 mg/1 1; NICOTINAMIDE MONONUCLEOTIDE 500 mg/1 1; WHITE PEPPER 50 mg/1 1
INACTIVE INGREDIENTS: ISOMALT; ERYTHRITOL; STEARIC ACID; HYDROXYPROPYL CELLULOSE, UNSPECIFIED; CALCIUM PALMITATE; MICROCRYSTALLINE CELLULOSE

Active ingredient

Resveratrol 400mg

β-Nicotinamide Mononucleotide 500mg

Piper nigrum extract 50mg

Warning

Not intended for children. Do not exceed the stated recommended daily dose. keep sealed in a cool, dry place away from excessive heat. Do not use if bottle seal is broken or missing.

Direction

As a dietary supplement, take one lozenge daily in the morning on an empty stomach or as direacted by your healthcare professional place one lozenge under the tongue to dissolve before swallowing.

Inactive ingredient

Isomalt, Erythritol, microcrystalline cellulose, natural flavour, stearic acid, Hydroxypropyl cellulose, calcium palmitate

Other information

Store in a dry place at room temperature